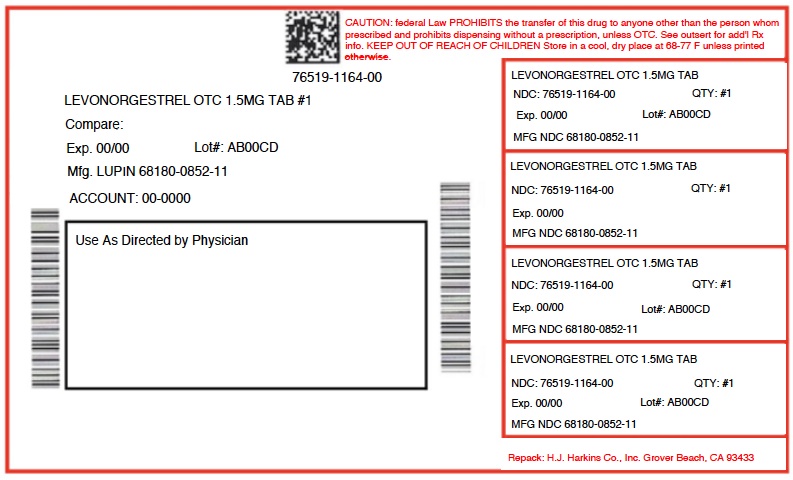 DRUG LABEL: LEVONORGESTREL
NDC: 76519-1164 | Form: TABLET
Manufacturer: H.J. Harkins Company, Inc.
Category: otc | Type: HUMAN OTC DRUG LABEL
Date: 20190918

ACTIVE INGREDIENTS: LEVONORGESTREL 1.5 mg/1 1
INACTIVE INGREDIENTS: LACTOSE MONOHYDRATE; MAGNESIUM STEARATE; POVIDONE K30; SILICON DIOXIDE; STARCH, CORN

1164 LEVONORGESTREL

ACTIVE INGREDIENT

Levonorgestrel USP 1.5 mg

PURPOSE

Emergency contraceptive

INDICATIONS AND USAGE

Use for women to reduce chance of pregnancy after unprotected sex (if a contraceptive failed or if you did not use birth control).

Allergy alert: Do not use if you have ever had an allergic reaction to levonorgestrel.

Sexually transmitted diseases (STDs) alert: This product does not protect against HIV/AIDS or other STDs

Do not use

if you are already pregnant (because it will not work)
for regular birth control

Ask a doctor or pharmacist before use if you are taking efavirenz (HIV medication) or rifampin (tuberculosis treatment) or medication for seizures (epilepsy). These medications may reduce the effectiveness of levonorgestrel.

When using this product you may have

menstrual changes
nausea
lower stomach (abdominal) pain
tiredness
headache
dizziness
breast pain
vomiting

Keep out of the reach of children.

In case of overdose, get medical help or contact a Poison Control center right away.

Directions

take as soon as possible within 72 hours (3 days) after unprotected sex. The sooner you take it the better it will work.
if you vomit within 2 hours after taking the medication, call a healthcare professional to find out if you should repeat the dose.

Other Information

read the instructions, warnings and enclosed product leaflet before use .
this product works mainly by preventing ovulation (egg release). It may also prevent fertilization of a released egg (joining of sperm and egg) or attachment of a fertilized egg to the uterus (implantation).
Do not use if carton is open or blister seal is broken or missing .
store at 25°C (77°C); excursions permitted to 15 to 30°C (59 to 86°C) [see USP Controlled Room temperature].

INACTIVE INGREDIENT

colloidal silicon dioxide, corn starch, lactose monohydrate, magnesium stearate, and povidone.